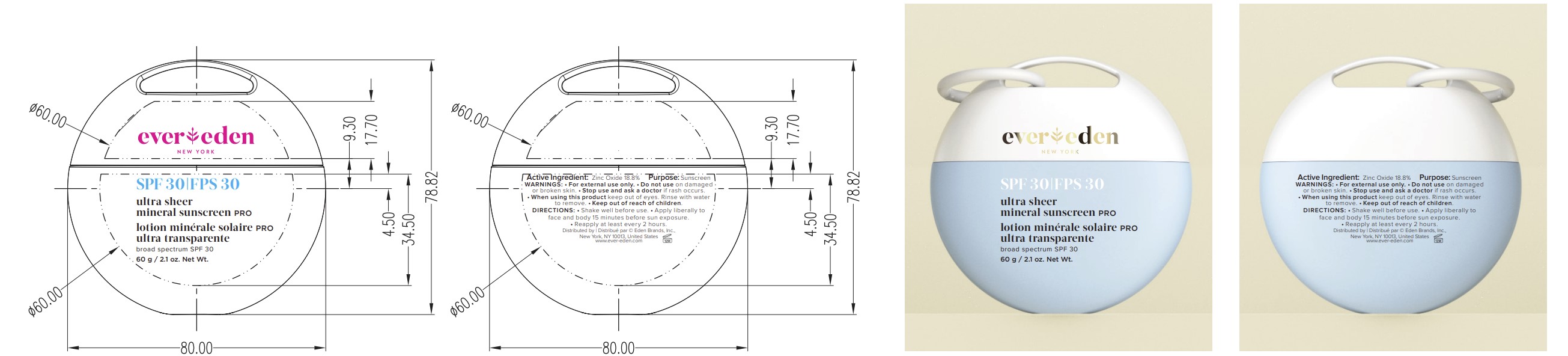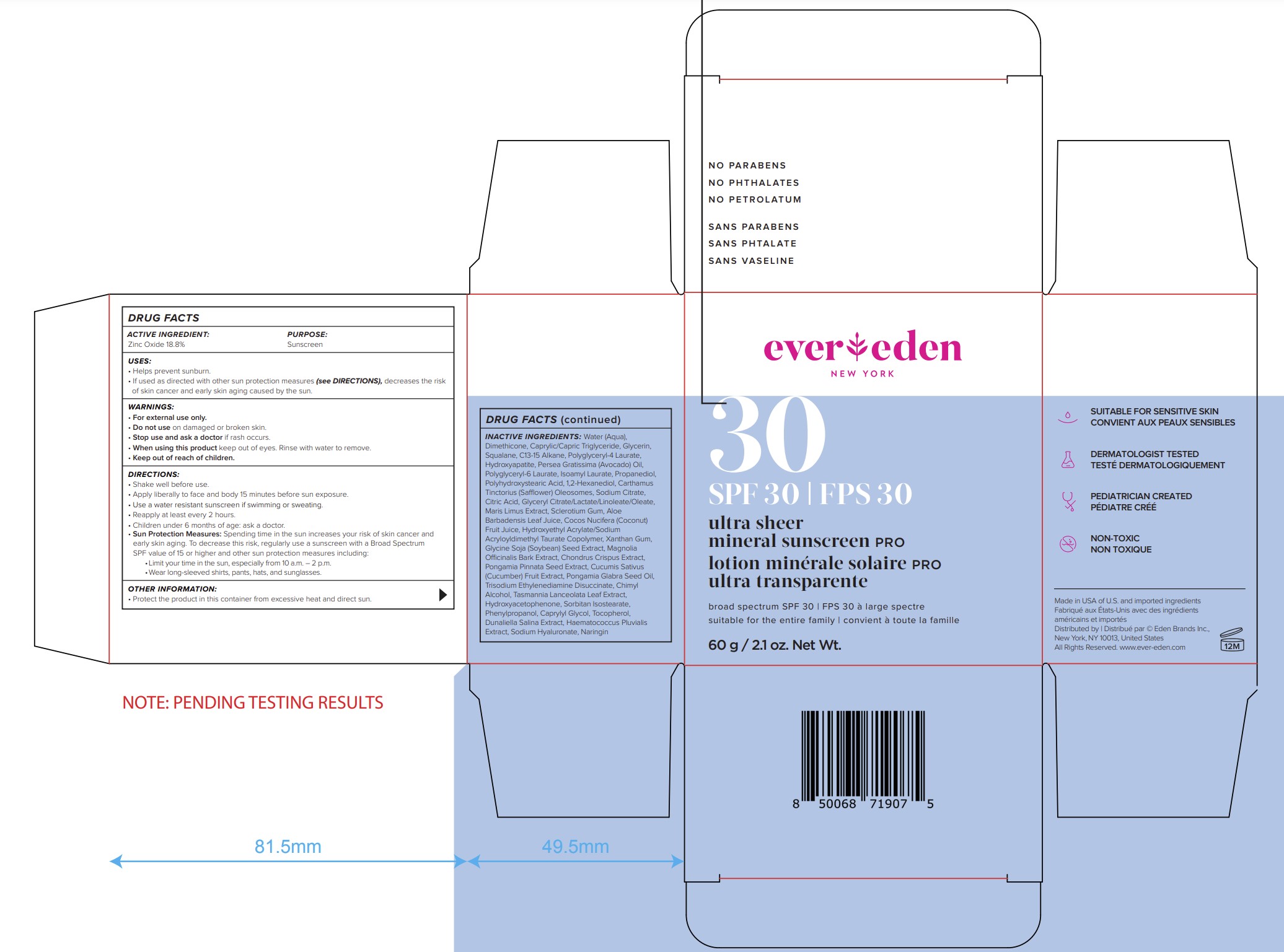 DRUG LABEL: Ultra sheer mineral sunscreen PRO SPF30
NDC: 72113-112 | Form: LOTION
Manufacturer: Eden Brands Inc.
Category: otc | Type: HUMAN OTC DRUG LABEL
Date: 20250214

ACTIVE INGREDIENTS: ZINC OXIDE 188 mg/1 g
INACTIVE INGREDIENTS: POLYHYDROXYSTEARIC ACID (2300 MW); CITRIC ACID MONOHYDRATE; DUNALIELLA SALINA; HYDROXYETHYL ACRYLATE/SODIUM ACRYLOYLDIMETHYL TAURATE COPOLYMER (100000 MPA.S AT 1.5%); KARUM SEED OIL; SQUALANE; CHIMYL ALCOHOL; PERSEA GRATISSIMA (AVOCADO) OIL; SCLEROTIUM GUM; COCOS NUCIFERA (COCONUT) FRUIT JUICE; XANTHAN GUM; POLYGLYCERYL-4 LAURATE; POLYGLYCERYL-6 LAURATE; 1,2-HEXANEDIOL; C13-15 ALKANE; GLYCERIN; DIMETHICONE; WATER; CAPRYLIC/CAPRIC TRIGLYCERIDE; TRISODIUM ETHYLENEDIAMINE DISUCCINATE; TASMANNIA LANCEOLATA LEAF; ISOAMYL LAURATE; PROPANEDIOL; SOYBEAN; CUCUMBER; HYDROXYACETOPHENONE; SORBITAN ISOSTEARATE; TOCOPHEROL; NARINGIN; HYDROXYAPATITE; CARTHAMUS TINCTORIUS (SAFFLOWER) OLEOSOMES; SODIUM CITRATE; GLYCERYL CITRATE/LACTATE/LINOLEATE/OLEATE; ALOE BARBADENSIS LEAF JUICE; PONGAMIA PINNATA SEED; PHENYLPROPANOL; MAGNOLIA OFFICINALIS BARK; CHONDRUS CRISPUS CARRAGEENAN; SODIUM HYALURONATE; CAPRYLYL GLYCOL; HAEMATOCOCCUS PLUVIALIS

ACTIVE INGREDIENT:

Zinc Oxide 18.8%

PURPOSE:

Sunscreen

USES:

• Helps prevent sunburn. • If used as directed with other sun protection measures (see DIRECTIONS), decreases the risk of skin cancer and early skin aging caused by the sun.

WARNINGS:

• For external use only

• Do not use on damaged or broken skin.

• Stop use and ask a doctor if rash occurs

When using this product keep out of eyes. Rinse with water to remove.

• Keep out of reach of children.

DIRECTIONS:

• Shake well before use.

• Apply liberally to face and body 15 minutes before sun exposure.

• Use a water resistant sunscreen if swimming or sweating.

• Reapply at least every 2 hours.

• Children under 6 months of age: ask a doctor.

• Sun Protection Measures: Spending time in the sun increases your risk of skin cancer and early skin aging. To decrease this risk, regularly use a sunscreen with a Broad Spectrum SPF value of 15 or higher and other sun protection measures including:

• Limit your time in the sun, especially from 10 a.m. – 2 p.m.

• Wear long-sleeved shirts, pants, hats, and sunglasses.

INACTIVE INGREDIENTS:

Water (Aqua), Dimethicone, Caprylic/Capric Triglyceride, Glycerin, Squalane, C13-15 Alkane, Polyglyceryl-4 Laurate, Hydroxyapatite, Persea Gratissima (Avocado) Oil, Polyglyceryl-6 Laurate, Isoamyl Laurate, Propanediol, Polyhydroxystearic Acid, 1,2-Hexanediol, Carthamus Tinctorius (Safflower) Oleosomes, Sodium Citrate, Citric Acid, Glyceryl Citrate/Lactate/Linoleate/Oleate, Maris Limus Extract, Sclerotium Gum, Aloe Barbadensis Leaf Juice, Cocos Nucifera (Coconut) Fruit Juice, Hydroxyethyl Acrylate/Sodium Acryloyldimethyl Taurate Copolymer, Xanthan Gum, Glycine Soja (Soybean) Seed Extract, Magnolia Officinalis Bark Extract, Chondrus Crispus Extract, Pongamia Pinnata Seed Extract, Cucumis Sativus (Cucumber) Fruit Extract, Pongamia Glabra Seed Oil, Trisodium Ethylenediamine Disuccinate, Chimyl Alcohol, Tasmannia Lanceolata Leaf Extract, Hydroxyacetophenone, Sorbitan Isostearate, Phenylpropanol, Caprylyl Glycol, Tocopherol, Dunaliella Salina Extract, Haematococcus Pluvialis Extract, Sodium Hyaluronate, Naringin